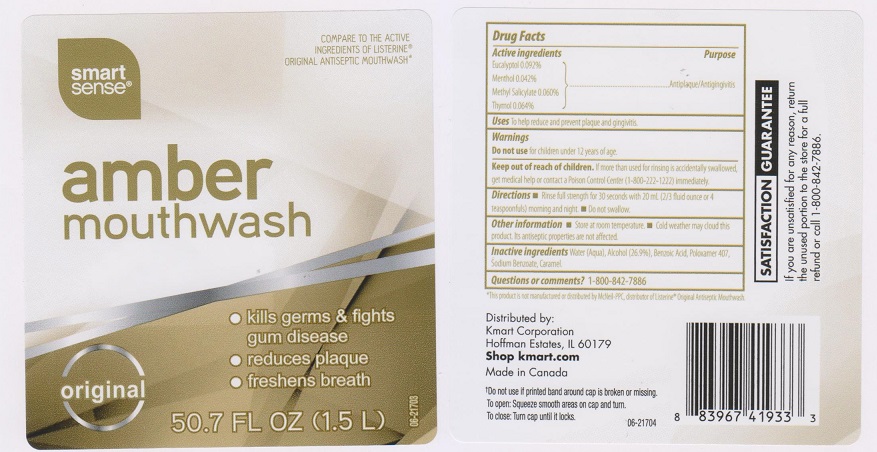 DRUG LABEL: Smart Sense
NDC: 49738-556 | Form: LIQUID
Manufacturer: Kmart Corporation
Category: otc | Type: HUMAN OTC DRUG LABEL
Date: 20170331

ACTIVE INGREDIENTS: EUCALYPTOL 0.92 mg/1 mL; MENTHOL 0.42 mg/1 mL; METHYL SALICYLATE 0.6 mg/1 mL; THYMOL 0.64 mg/1 mL
INACTIVE INGREDIENTS: WATER; ALCOHOL; BENZOIC ACID; POLOXAMER 407; SODIUM BENZOATE; CARAMEL

Drug Facts

Active ingredients

Eucalyptol 0.092%, Menthol 0.042%, Methyl Salicylate 0.060%, Thymol 0.064%

Purpose

Antiplaque/Antigingivitis

Uses

to help reduce and prevent plaque and gingivitis.

Warnings

Do not use for children under 12 years of age.

Keep out of reach of children.

If more than used for rinsing is accidentally swallowed, get medical help or contact a Poison Control Center (1-800-222-1222) immediately.

Directions

- Rinse full strength for 30 seconds with 20 mL (2/3 fluid ounce or 4 teaspoonfuls) morning and night
- Do not swallow

Other information

- Store at room temperature.
- Cold weather may cloud this product. Its antiseptic properties are not affected.

Inactive ingredients

Water (Aqua), Alcohol (26.9%), Benzoic Acid, Poloxamer 407, Sodium Benzoate, Caramel.

Questions or comments?

1-800-842-7886